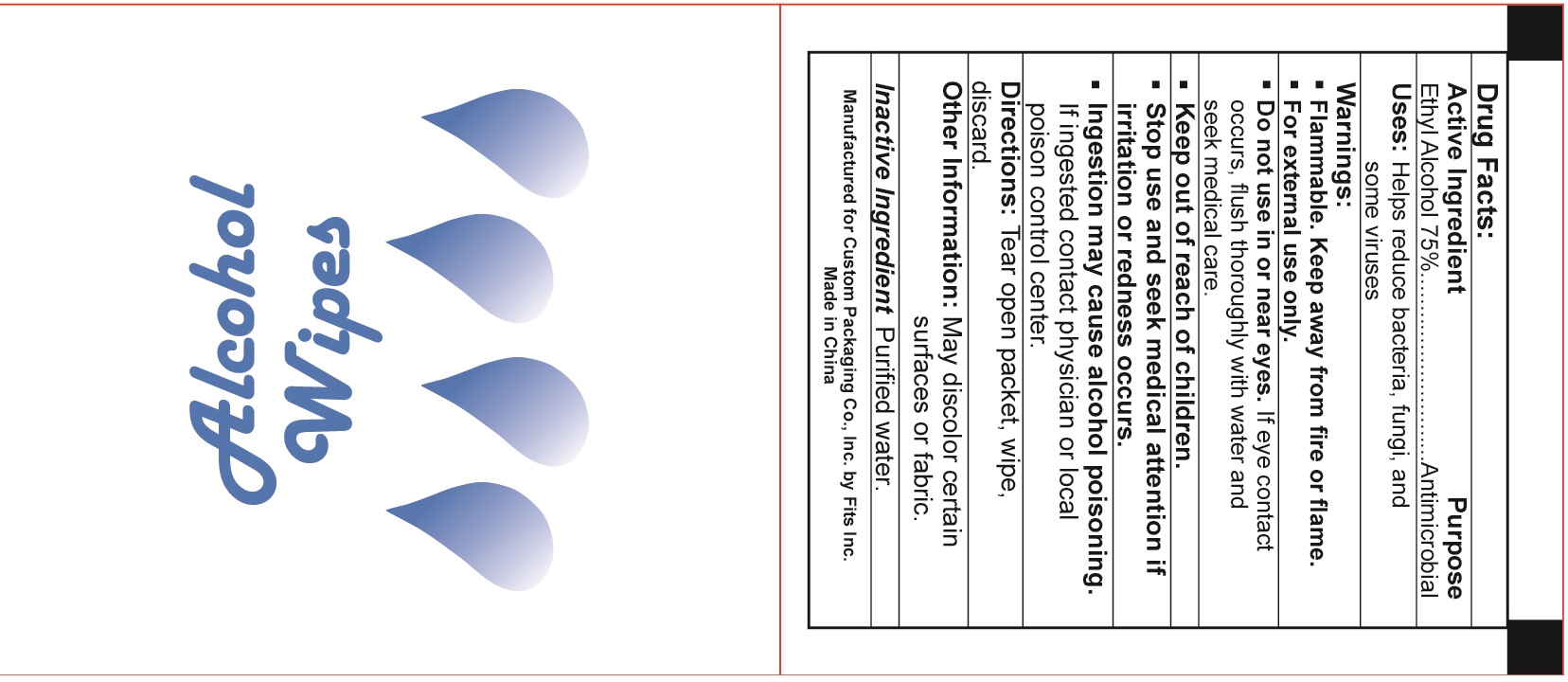 DRUG LABEL: Alcohol Wipes
NDC: 82447-102 | Form: SWAB
Manufacturer: Meizhou Jubona Technology Co., Ltd.
Category: otc | Type: HUMAN OTC DRUG LABEL
Date: 20211213

ACTIVE INGREDIENTS: Alcohol 75 g/100 g
INACTIVE INGREDIENTS: water

DRUG FACTS

Active Ingredient

Ethly Alcohol ................ 75%

Purpose

Antimicrobial

Uses:

Helps reduce bacteria,fungi and some viruses.

Warnings

DO NOT USE

Flammable. Keep away from fire or flame.

For external use only.

- Do not use in or near eyes. If eye contact occurs ,flush thoroughl with water and seek medical care.
- Stop use and seek medical attentionif irritation or redness occurs.
- Ingestion may cause alcohol poisoning. If ingested contact physician or local poison control center.

Other Information:

May discolor certain surfaces or fabric.

Keep out of reach of children.

if swallowed get medical help or contact a Poison Control Center right away.

Directions

Tear open packet, wipe discard.

Inactive Ingredients:

Purified Water